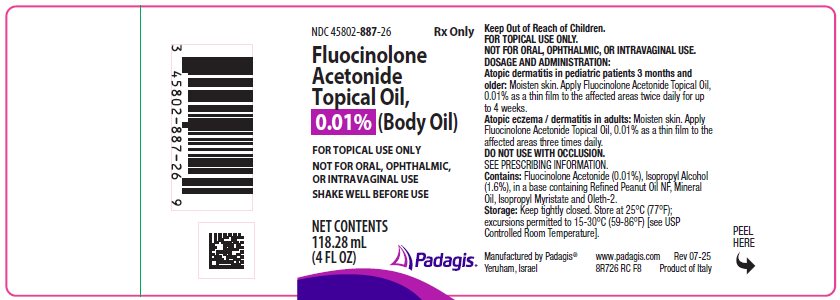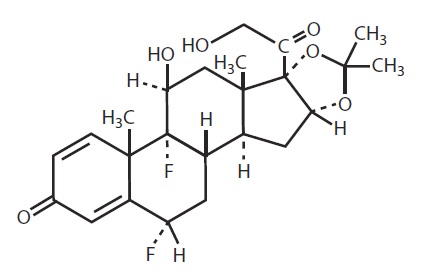 DRUG LABEL: fluocinolone acetonide
NDC: 45802-887 | Form: OIL
Manufacturer: Padagis Israel Pharmaceuticals Ltd
Category: prescription | Type: HUMAN PRESCRIPTION DRUG LABEL
Date: 20250731

ACTIVE INGREDIENTS: FLUOCINOLONE ACETONIDE 0.01 mg/100 mL
INACTIVE INGREDIENTS: ISOPROPYL ALCOHOL; ISOPROPYL MYRISTATE; LIGHT MINERAL OIL; OLETH-2

HIGHLIGHTS OF PRESCRIBING INFORMATION

These highlights do not include all the information needed to use FLUOCINOLONE ACETONIDE TOPICAL OIL safely and effectively. See full prescribing information for FLUOCINOLONE ACETONIDE TOPICAL OIL.
FLUOCINOLONE ACETONIDE topical oil (body oil)
Initial U.S. Approval: 1988

1 INDICATIONS AND USAGE

Fluocinolone acetonide topical oil is a corticosteroid indicated for the topical treatment of:

- atopic dermatitis in adults (1)
- moderate to severe atopic dermatitis in pediatric patients 3 months of age and older (1)

2 DOSAGE AND ADMINISTRATION

- Fluocinolone acetonide topical oil is not for oral, ophthalmic, or intravaginal use. (2.1)
- Do not use on face or intertriginous areas. (2.1)
- Adult patients: Apply to affected areas 3 times daily. (2.2)
- Pediatric patients: Moisten skin and apply to affected areas twice daily for up to 4 weeks. (2.3)

3 DOSAGE FORMS AND STRENGTHS

Fluocinolone Acetonide Topical Oil, 0.01% (Body Oil) is a topical oil containing 0.01% fluocinolone acetonide supplied in bottles containing 4 fluid ounces. (3)

4 CONTRAINDICATIONS

None. (4)

5 WARNINGS AND PRECAUTIONS

- Endocrine System Adverse Reactions:
  - Topical corticosteroids can produce reversible hypothalamic-pituitary-adrenal (HPA) axis suppression, Cushing’s syndrome, hyperglycemia, and glucosuria. (5.1)
  - Pediatric patients may be more susceptible to systemic toxicity from equivalent doses. (5.1, 8.4)
  - Systemic absorption may require evaluation for HPA axis suppression. Potent corticosteroids use on large areas, prolonged use, occlusive use, altered skin barrier, liver failure, and young age may increase systemic absorption. Modify use should HPA axis suppression develop. (5.1)
- Local Adverse Reactions: Local adverse reactions may include atrophy, striae, irritation, acneiform eruptions, hypopigmentation, and allergic contact dermatitis and may be more likely with occlusive use or more potent corticosteroids. (5.2, 6.1)
- Ophthalmic Adverse Reactions: May increase the risks of glaucoma and posterior subcapsular cataract. Avoid contact of fluocinolone acetonide topical oil with eyes. Advise patients to report any visual symptoms and consider referral to an ophthalmologist for evaluation. (5.3)

6 ADVERSE REACTIONS

The most common adverse reactions (≥ 5%) were cough (20%), rhinorrhea (13%), pyrexia (10%), telangiectasia (7%), nasopharyngitis (7%), and hypopigmentation (7%). (6.1, 6.2)

To report SUSPECTED ADVERSE REACTIONS, contact Padagis® at 1-866-634-9120 or FDA at 1-800-FDA-1088 or www.fda.gov/medwatch.

FULL PRESCRIBING INFORMATION

1 INDICATIONS AND USAGE

Fluocinolone acetonide topical oil is indicated for the topical treatment of:

- atopic dermatitis in adults
- moderate to severe atopic dermatitis in pediatric patients 3 months of age and older

2 DOSAGE AND ADMINISTRATION

2.1 Important Administration Instructions

Fluocinolone acetonide topical oil is for topical use only. Not for oral, ophthalmic, or intravaginal use.

Apply the least amount of fluocinolone acetonide topical oil needed to cover the affected areas. Discontinue use when control of disease is achieved within 2 weeks or contact the healthcare provider if no improvement is seen within 2 weeks.

Do not use on the face, axillae, or groin unless directed by the healthcare provider. Do not apply to intertriginous areas due to the increased risk of local adverse reactions [see Adverse Reactions (6) and Use in Specific Populations (8.4)].

Do not apply to the diaper area; diapers or plastic pants may constitute occlusive use [see Warnings and Precautions (5.1)].

2.2 Recommended Dosage in Adults

Apply fluocinolone acetonide topical oil as a thin film to the affected areas three times daily.

2.3 Recommended Dosage in Pediatric Patients

Moisten skin and apply fluocinolone acetonide topical oil as a thin film to the affected areas twice daily for up to four weeks.

3 DOSAGE FORMS AND STRENGTHS

Fluocinolone Acetonide Topical Oil, 0.01% (Body Oil) is a topical oil containing 0.01% fluocinolone acetonide, supplied in bottles containing 4 fluid ounces.

4 CONTRAINDICATIONS

None.

5 WARNINGS AND PRECAUTIONS

5.1 Endocrine System Adverse Reactions

Systemic absorption of topical corticosteroids can produce reversible hypothalamic-pituitary-adrenal (HPA) axis suppression with the potential for glucocorticosteroid insufficiency. Cushing’s syndrome, hyperglycemia, and glucosuria can result from systemic absorption of topical corticosteroids.

HPA axis suppression and Cushing’s syndrome have been reported in pediatric patients receiving topical corticosteroids. Manifestations of adrenal suppression in pediatric patients include linear growth retardation, delayed weight gain, low plasma cortisol levels, and subnormal response to ACTH stimulation. Pediatric patients may be more susceptible to systemic toxicity from equivalent doses due to their larger skin surface to body mass ratios [see Use in Specific Populations (8.4)].

Conditions which increase systemic absorption include the use of more potent corticosteroids, use over large surface areas, use over prolonged periods, use of occlusive dressings, altered skin barrier, liver failure, and young age. Use of more than one corticosteroid-containing product at the same time may increase total systemic corticosteroid exposure. Because of the potential for systemic absorption, use of topical corticosteroids may require that patients be periodically evaluated for HPA axis suppression. The ACTH stimulation test may be helpful in evaluating patients for HPA axis suppression.

If HPA axis suppression is documented, reduce the frequency of application or discontinue fluocinolone acetonide topical oil, or substitute with a less potent corticosteroid. Manifestations of adrenal insufficiency may require supplemental systemic corticosteroids. Recovery of HPA axis function is generally prompt upon discontinuation of topical corticosteroids.

5.2 Local Adverse Reactions

Local adverse reactions may occur with use of topical corticosteroids, including fluocinolone acetonide topical oil, and may be more likely to occur with occlusive use, prolonged use or use of higher potency corticosteroids. Some local adverse reactions may be irreversible. Reactions may include atrophy, striae, telangiectasias, burning, itching, irritation, dryness, folliculitis, acneiform eruptions, hypopigmentation, perioral dermatitis, allergic contact dermatitis, secondary infection, and miliaria [see Adverse Reactions (6.1)].

5.3 Ophthalmic Adverse Reactions

Use of topical corticosteroids may increase the risks of glaucoma and posterior subcapsular cataract. Glaucoma and cataracts have been reported in postmarketing experience with the use of topical corticosteroid products. Avoid contact of fluocinolone acetonide topical oil with eyes. Advise patients to report any visual symptoms and consider referral to an ophthalmologist for evaluation.

5.4 Allergic Contact Dermatitis

Use of topical corticosteroids can cause allergic contact dermatitis. Allergic contact dermatitis to any component of topical corticosteroids is usually diagnosed by a failure to heal rather than a clinical exacerbation. Clinical diagnosis of allergic contact dermatitis can be confirmed by patch testing.

5.5 Concomitant Skin Infections

Use of topical corticosteroids may delay healing or worsen concomitant skin infections. Treat concomitant skin infections with an appropriate antimicrobial agent. If the infection persists unchanged, discontinue fluocinolone acetonide topical oil until the infection has been adequately treated.

5.6 Use in Peanut-Sensitive Individuals

Use caution in prescribing fluocinolone acetonide topical oil for peanut-sensitive individuals [see Description (11)].

Should signs of hypersensitivity present (wheal and flare reactions, pruritus, or other manifestations), or should disease exacerbations occur, discontinue fluocinolone acetonide topical oil immediately and institute appropriate therapy.

6 ADVERSE REACTIONS

The following serious adverse reactions are discussed in more detail in other sections of the labeling:

- Endocrine System Adverse Reactions [see Warnings and Precautions (5.1), Use in Specific Populations (8.4)]
- Local Adverse Reactions [see Warnings and Precautions (5.2)]
- Ophthalmic Adverse Reactions [see Warnings and Precautions (5.3)]

6.1 Clinical Studies Experience

Because clinical trials are conducted under widely varying conditions, adverse reaction rates observed in the clinical trials of a drug cannot be directly compared to rates in the clinical trials of another drug and may not reflect the rates observed in practice.

An open-label trial was conducted in 58 pediatric subjects 2 years to 12 years of age with moderate to severe atopic dermatitis to evaluate the safety of fluocinolone acetonide topical oil when applied to the face twice daily for 4 weeks. Adverse reactions reported by ≥2% of pediatric subjects treated with fluocinolone acetonide topical oil are shown in Table 1.

Table 1: Adverse Reactions in ≥2% of Pediatric Subjects 2 Years to 12 Years of Age with Moderate to Severe Atopic Dermatitis, Treated with Fluocinolone Acetonide Topical Oil (Body Oil), N=58

Adverse Reaction (AR)* | n (%) | Day 14 | Day 28** | Day 56***
Any AE | 15 (26) | 6 (10) | 7 (12) | 7 (12)
Telangiectasia | 5 (9) | 3 (5) | 4 (7) | 2 (4)
Erythema | 3 (5) |  |  | 3 (5)
Itching | 3 (5) |  |  | 3 (5)
Irritation | 3 (5) |  |  | 3 (5)
Burning | 3 (5) |  |  | 3 (5)
Hypopigmentation | 2 (4) | 2 (4)
Shiny skin | 1 (2) |  | 1 (2)
Secondary atopic dermatitis | 1 (2) |  |  | 1 (2)
Papules and pustules | 1 (2) |  |  | 1 (2)
Keratosis pilaris | 1 (2) |  |  | 1 (2)
Folliculitis | 1 (2) |  | 1 (2)
Facial herpes simplex | 1 (2) | 1 (2)
Acneiform eruption | 1 (2) |  | 1 (2)
Ear infection | 1 (2) |  | 1 (2)

*The number of individual adverse reactions reported does not necessarily reflect the number of individual subjects, since one subject could have multiple reports of an adverse reaction.

**End of Treatment

***Four Weeks Post Treatment

An open-label safety trial was conducted in 29 pediatric subjects 3 months to 2 years of age to assess the HPA axis by ACTH stimulation testing following use of fluocinolone acetonide topical oil twice daily for 4 weeks. The trial included 7 subjects ages 3 to 6 months, 7 subjects ages > 6 to 12 months, and 15 subjects ages > 12 months to 2 years. All subjects had moderate to severe atopic dermatitis with disease involvement on at least 20% body surface area (BSA). Eleven (11) subjects had baseline BSA involvement of 50% to 75% and 7 subjects had BSA involvement of greater than 75% [see Use in Specific Populations (8.4)]. The most common adverse reactions reported in the study (≥2%) are shown in Table 2.

Table 2: Adverse Reactions in ≥ 2% of Pediatric Subjects 3 Months to 2 Years of Age with Moderate to Severe Atopic Dermatitis, Treated with Fluocinolone Acetonide Topical Oil (Body Oil), N=30*

Adverse Reaction | n (%)
Cough | 6 (20)
Rhinorrhea | 4 (13)
Pyrexia | 3 (10)
Nasopharyngitis | 2 (7)
Hypopigmentation | 2 (7)
Abscess | 1 (3)
Atopic Dermatitis | 1 (3)
Eczema | 1 (3)
Hyperpigmentation | 1 (3)
Molluscum | 1 (3)
Rash | 1 (3)
Diarrhea | 1 (3)
Otitis Media | 1 (3)
URI | 1 (3)
Vomiting | 1 (3)

*Includes one subject who withdrew at Week 2

6.2 Postmarketing Experience

The following adverse reactions have been identified during post-approval use of products containing topical corticosteroids. Because postmarketing adverse reactions are reported voluntarily from a population of uncertain size, it is not always possible to reliably estimate their frequency or establish a causal relationship to drug exposure.

    - Endocrine Disorders: HPA axis suppression and Cushing’s syndrome [see Use in Specific Populations (8.4)]
    - Eye Disorders: glaucoma and cataracts [see Warnings and Precautions (5.3)]
    - Nervous System Disorders: intracranial hypertension including bulging fontanelles, headaches, and bilateral papilledema [see Use in Specific Populations (8.4)]

8 USE IN SPECIFIC POPULATIONS

8.1 Pregnancy

Risk Summary

Available data from case reports, case series, and observational studies on fluocinolone acetonide use in pregnant women have not identified a drug-associated risk of major birth defects, miscarriage or adverse maternal or fetal outcomes. Observational studies suggest maternal use of high to super-high potency topical steroids may be associated with an increased risk of low birthweight infants. Advise pregnant women to use fluocinolone acetonide topical oil on the smallest area of skin and for the shortest duration possible.

Corticosteroids can cause fetal malformations in laboratory animals when administered systemically at relatively low dosage levels. Some corticosteroids cause fetal malformations after dermal application in laboratory animals.

The background risk of major birth defects and miscarriage for the indicated population is unknown. All pregnancies have a background risk of birth defect, loss, or other adverse outcomes. In the U.S. general population, the estimated background risk of major birth defects and miscarriage in clinically recognized pregnancies is 2 to 4% and 15 to 20%, respectively.

8.2 Lactation

Risk Summary

There is no information regarding the presence of fluocinolone acetonide in breast milk or its effects on the breastfed infant or on milk production. It is not known whether topical administration of corticosteroids could result in sufficient systemic absorption to produce detectable quantities in breast milk. To minimize potential exposure to the breastfed infant via breast milk, use fluocinolone acetonide topical oil on the smallest area of skin and for the shortest duration possible while breastfeeding. Advise breastfeeding women not to apply fluocinolone acetonide topical oil directly to the nipple and areola to avoid direct infant exposure [see Warnings and Precautions (5.1) and Use in Specific Populations (8.4)].

The developmental and health benefits of breastfeeding should be considered along with the mother's clinical need for fluocinolone acetonide topical oil and any potential adverse effects on the breastfed infant from fluocinolone acetonide topical oil or from the underlying maternal condition.

8.4 Pediatric Use

The safety and effectiveness of fluocinolone acetonide topical oil for the topical treatment of moderate to severe atopic dermatitis have been established in pediatric patients aged 3 months and older for up to 4 weeks.

Safety and effectiveness of fluocinolone acetonide topical oil in pediatric patients with atopic dermatitis below the age of 3 months have not been established.

Systemic Adverse Reactions in Pediatric Patients

HPA axis suppression, Cushing’s syndrome, and intracranial hypertension have been reported in pediatric patients receiving topical corticosteroids. Manifestations of adrenal suppression in children include linear growth retardation, delayed weight gain, low plasma cortisol levels, and subnormal response to ACTH stimulation. Manifestations of intracranial hypertension include bulging fontanelles, headaches, and bilateral papilledema.

Because of a higher ratio of skin surface area to body mass, pediatric patients are at a greater risk for systemic adverse reactions than are adults when treated with topical corticosteroids [see Warnings and Precautions (5.1)].

Evaluation in Peanut-Sensitive Pediatric Patients

A clinical trial was conducted to assess the safety of fluocinolone acetonide topical oil, which contains refined peanut oil, on pediatric subjects with known peanut allergies. The study enrolled 13 pediatric subjects with atopic dermatitis, 6 to 17 years of age. Of the 13 subjects, 9 were Radioallergosorbent Test (RAST) positive to peanuts and 4 had no peanut sensitivity (controls). The trial evaluated the subjects' responses to both prick test and patch test utilizing refined peanut oil, fluocinolone acetonide topical oil and histamine/saline controls. Subjects were also treated with fluocinolone acetonide topical oil twice daily for 7 days. Prick test and patch test results for all 13 patients were negative to fluocinolone acetonide topical oil and the refined peanut oil. One of the 9 peanut-sensitive patients experienced an exacerbation of atopic dermatitis after 5 days of fluocinolone acetonide topical oil.

Evaluation in Pediatric Patients 2 to 6 years old

Use of fluocinolone acetonide topical oil in pediatric patients 2 to 6 years old is supported by open-label safety trials conducted in 33 pediatric subjects (20 subjects ages 2 to 6 years, 13 subjects ages 7 to 12 years) with moderate to severe stable atopic dermatitis. Baseline body surface area involvement was 50% to 75% in 15 subjects and greater than 75% in 18 subjects. Subjects were treated with fluocinolone acetonide topical oil twice daily for 4 weeks. Morning pre-stimulation cortisol and post-ACTH stimulation cortisol levels were obtained in each subject at the beginning of the trial and at the end of 4 weeks of treatment. At the end of treatment, 4 out of 18 subjects aged 2 to 5 years showed low pre-stimulation cortisol levels (3.2 to 6.6 µg/dL; normal: cortisol > 7µg/dL) but all had normal responses to 0.25 mg of ACTH stimulation (cortisol > 18 µg/dL) [see Clinical Pharmacology (12.2)].

Evaluation in Pediatric Patients 3 months to 2 years old

Use of fluocinolone acetonide topical oil in pediatric patients 3 months to 2 years old is supported by an open-label safety trial conducted in 29 pediatric subjects (7 subjects ages 3 to 6 months, 7 subjects ages > 6 to 12 months, and 15 subjects ages > 12 months to 2 years) to assess the HPA axis by ACTH stimulation testing following use of fluocinolone acetonide topical oil twice daily for 4 weeks [see Adverse Reactions (6.1)]. Morning pre-stimulation and post-ACTH stimulation cortisol levels were obtained in each subject at the beginning of the trial and at the end of 4 weeks of treatment. All subjects had normal responses to 0.125 mg of ACTH stimulation (cortisol > 18 µg/dL) [see Clinical Pharmacology (12.2)].

11 DESCRIPTION

Fluocinolone Acetonide Topical Oil, 0.01% (Body Oil) contains fluocinolone acetonide [(6α, 11β, 16α)-6,9-difluoro-11,21-dihydroxy-16,17[(1-methylethylidene) bis(oxy)]-pregna-1,4-diene-3,20-dione, cyclic 16,17 acetal with acetone], a synthetic corticosteroid for topical dermatologic use. Chemically, fluocinolone acetonide is C24H30F2O6. It has the following structural formula:

Fluocinolone acetonide has a molecular weight of 452.50. It is a white crystalline powder that is odorless, stable in light, and melts at 270°C with decomposition; soluble in alcohol, acetone and methanol; slightly soluble in chloroform; insoluble in water.

Each gram of Fluocinolone Acetonide Topical Oil, 0.01% (Body Oil) contains approximately 0.11 mg of fluocinolone acetonide in a blend of oils, which contains isopropyl alcohol, isopropyl myristate, light mineral oil, oleth-2 and refined peanut oil.

Fluocinolone acetonide topical oil is formulated with 48% refined peanut oil. The bulk refined peanut oil, used in fluocinolone acetonide topical oil is heated just below 232°C (450°F) for at least 15 minutes.

12 CLINICAL PHARMACOLOGY

12.1 Mechanism of Action

Corticosteroids play a role in cellular signaling, immune function, inflammation, and protein regulation; however, the precise mechanism of action in atopic dermatitis is unknown.

12.2 Pharmacodynamics

Vasoconstrictor Assay

Fluocinolone acetonide topical oil is in the low to medium range of potency as compared with other topical corticosteroids in vasoconstrictor studies. However, similar blanching scores do not necessarily imply therapeutic equivalence.

Hypothalamic-Pituitary-Adrenal (HPA) Axis Suppression

HPA axis suppression was evaluated in 29 pediatric subjects 3 months to 2 years old (7 subjects ages 3 to 6 months, 7

subjects ages > 6 to 12 months, and 15 subjects ages > 12 months to 2 years) and 33 pediatric subjects 2 years to 12 years old (20 subjects ages 2 to 6 years, 13 subjects ages 7 to 12 years) with moderate to severe atopic dermatitis. Subjects were treated with fluocinolone acetonide topical oil twice daily for 4 weeks. Morning pre-stimulation and post-ACTH stimulation cortisol levels were obtained in each subject at the beginning of the trial and at the end of 4 weeks of treatment. In subjects 3 months to 2 years old, all subjects had normal responses to 0.125 mg of ACTH stimulation (cortisol > 18 µg/dL). In subjects 2 to 12 years old, 4 out of 18 subjects 2 to 5 years old showed low pre-stimulation cortisol levels (3.2 to 6.6 µg/dL; normal: cortisol > 7µg/dL) but all had normal responses to 0.25 mg of ACTH stimulation (cortisol > 18 µg/dL) at the end of treatment [see Warnings and Precautions (5.1) and Use in Specific Populations (8.4)].

12.3 Pharmacokinetics

Topical corticosteroids can be absorbed from intact healthy skin. The extent of percutaneous absorption of topical corticosteroids is determined by many factors, including the product formulation and the integrity of the epidermal barrier. Occlusion, inflammation and/or other disease processes in the skin may increase percutaneous absorption.

The use of pharmacodynamic endpoints for assessing the systemic exposure of topical corticosteroids may be necessary due to the fact that circulating levels are often below the level of detection. Once absorbed through the skin, topical corticosteroids are metabolized primarily in the liver, and are then excreted by the kidneys. Some corticosteroids and their metabolites are also excreted in the bile.

13 NONCLINICAL TOXICOLOGY

13.1 Carcinogenesis, mutagenesis, impairment of fertility

No carcinogenicity, genotoxicity, or fertility studies were conducted with fluocinolone acetonide topical oil. However, some corticosteroids are genotoxic in various genotoxicity tests (i.e., the in vitro human peripheral blood lymphocyte chromosome aberration assay with metabolic activation, the in vivo mouse bone marrow micronucleus assay, the Chinese hamster micronucleus test, and the in vitro mouse lymphoma gene mutation assay).

16 HOW SUPPLIED / STORAGE AND HANDLING

Fluocinolone Acetonide Topical Oil, 0.01% (Body Oil) (NDC 45802-887-26) is supplied in bottles containing 4 fluid ounces.

Storage: Keep tightly closed. Store at 20°-25°C (68°-77°F); excursions permitted to 15°-30°C (59°-86°F) [see USP Controlled Room Temperature].

PATIENT COUNSELING INFORMATION

Administration Instructions

Advise patients that fluocinolone acetonide topical oil is for topical use only [see Dosage and Administration (2.1)].

Advise patients to not to apply fluocinolone acetonide topical oil under occlusion unless directed by their healthcare provider. Instruct patients not to apply fluocinolone acetonide topical oil to the diaper area as diapers or plastic pants may constitute occlusive use [see Dosage and Administration (2.1)].

Advise patients to avoid use of fluocinolone acetonide topical oil on the face, axillae, or groin unless directed by their healthcare provider [see Dosage and Administration (2.1)].

Advise patients to discontinue therapy when control of disease is achieved. Instruct patients to contact their healthcare provider if no improvement is seen within 2 weeks [see Dosage and Administration (2.1)].

Endocrine System Adverse Reactions

Instruct patients not to use other corticosteroid-containing products while using fluocinolone acetonide topical oil without first consulting their healthcare provider [see Warnings and Precautions (5.1)].

Ophthalmic Adverse Reactions

Advise patients to avoid contact with the eyes and in case of contact, wash eyes liberally with water. Instruct patients to tell their healthcare provider if they develop any visual symptoms [see Warnings and Precautions (5.3)].

Pregnancy and Lactation

Advise patients to use fluocinolone acetonide topical oil on the smallest area of skin and for the shortest duration possible while pregnant or breastfeeding. Advise patients that are breastfeeding not to apply fluocinolone acetonide topical oil directly to the nipple and areola to avoid direct infant exposure [see Use in Specific Populations (8.1 and 8.2)].

Manufactured by Padagis®,

Yeruham, Israel

8R726 RC F8

PACKAGE/LABEL PRINCIPAL DISPLAY PANEL

NDC 45802-887-26

Rx Only

Fluocinolone Acetonide Topical Oil, 0.01% (Body Oil)

FOR TOPICAL USE ONLY

NOT FOR ORAL, OPHTHALMIC, OR INTRAVAGINAL USE

SHAKE WELL BEFORE USE

NET CONTENTS

118.28 mL

(4 FL OZ)